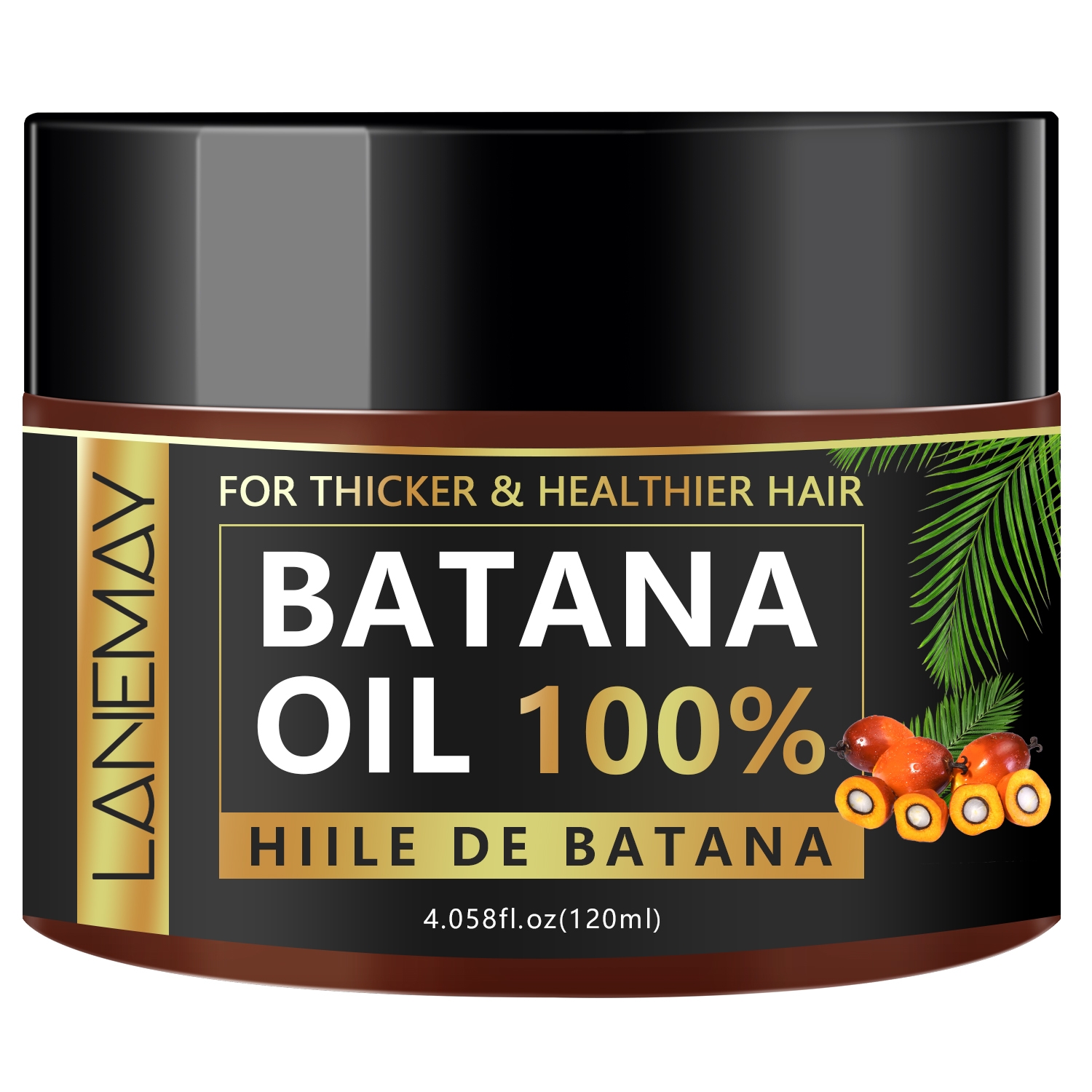 DRUG LABEL: Batana Oil Hair Mask
NDC: 84025-225 | Form: CREAM
Manufacturer: Guangzhou Yanxi Biotechnology Co., Ltd
Category: otc | Type: HUMAN OTC DRUG LABEL
Date: 20241021

ACTIVE INGREDIENTS: SORBITOL 6 mg/120 mL; DIMETHICONE 4 mg/120 mL
INACTIVE INGREDIENTS: WATER

DOSAGE AND ADMINISTRATION

Apply generously to wet hair after shampooing.Leave on for 3-5 minutes,then rinse thoroughly.

WARNINGS

Keep out of children

INACTIVE INGREDIENT

Aqua

INDICATIONS AND USAGE

For daily hair care

Keep out of children

PURPOSE

Nourish scalp and deeply condition hair